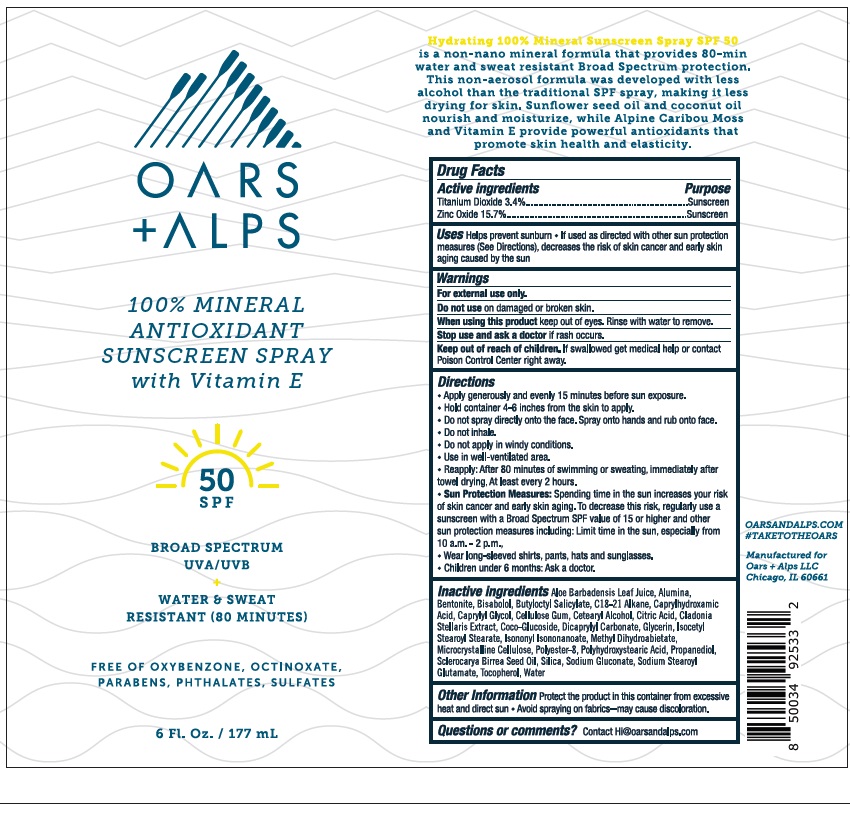 DRUG LABEL: Oars and Alps SPF 50 100% Mineral Antioxidant Sunscreen
NDC: 83046-369 | Form: SPRAY
Manufacturer: Oars and Alps LLC
Category: otc | Type: HUMAN OTC DRUG LABEL
Date: 20241220

ACTIVE INGREDIENTS: ZINC OXIDE 15.7 g/100 mL; TITANIUM DIOXIDE 3.4 g/100 mL
INACTIVE INGREDIENTS: GLYCERIN; SCLEROCARYA BIRREA SEED OIL; BENTONITE; CAPRYLYL GLYCOL; ISONONYL ISONONANOATE; POLYESTER-8 (1400 MW, CYANODIPHENYLPROPENOYL CAPPED); SILICON DIOXIDE; DICAPRYLYL CARBONATE; METHYL DIHYDROABIETATE; POLYHYDROXYSTEARIC ACID (2300 MW); SODIUM STEAROYL GLUTAMATE; WATER; CLADONIA RANGIFERINA WHOLE; C18-C21 ALKANE; CAPRYLHYDROXAMIC ACID; CETOSTEARYL ALCOHOL; TOCOPHEROL; COCO GLUCOSIDE; ALOE VERA LEAF; ALUMINUM OXIDE; BUTYLOCTYL SALICYLATE; PROPANEDIOL; MICROCRYSTALLINE CELLULOSE; CARBOXYMETHYLCELLULOSE SODIUM, UNSPECIFIED; LEVOMENOL; CITRIC ACID MONOHYDRATE; ISOCETYL STEAROYL STEARATE; SODIUM GLUCONATE

Oars & Alps SPF 50 100% Mineral Antioxidant Sunscreen Spray

ACTIVE INGREDIENT

Titanium Dioxide - 3.4%

Zinc Oxide - 15.7%

PURPOSE

Sunscreen

Uses

• Helps prevent sunburn

• If used as directed with other sun protection measures (see Directions), decreases the risk of skin cancer and early skin aging caused by the sun.

WARNINGS

- For external use only.
- Do not use on damaged or broken skin.
- When using this product keep out of eyes. Rinse with water to remove.
- Stop use and ask a doctor if rash occurs.

Keep out of reach of children. If swallowed, get medical help or contact a Poison Control Center right away.

Directions

- Apply generously and evenly 15 minutes before sun exposure
- Hold container 4-6 inches from the skin to apply
- Do not spray directly onto the face. Spray onto hands and rub onto face. Do not inhale.
- Do not apply in windy conditions.
- Use in well ventilated area.
- Reapply: After 80 minutes of swimming or sweating, immedately after towl drying, at least every 2 hours.
- Sun Protection Measures: Spending time in the sun increases your risk of skin cancer and early skin aging. To decrease this risk, regularly use a sunscreen with a Broad Spectrum SPF value of 15 or higher and other sun protection measures including: • Limit time in the sun especially from 10 a.m. – 2 p.m. • Wear long-sleeved shirts, pants, hats, and sunglasses.
- Children under six months: Ask a doctor.

INACTIVE INGREDIENT

Aloe Barbadensis Leaf Juice, Alumina, Bentonite, Bisabolol, Butyloctyl Salicylate, C18-21 Alkane, Caprylhydroxamic Acid, Caprylyl Glycol, Cellulose Gum, Cetearyl Alcohol, Citric Acid, Cladonia Stellaris Extract, Coco-Glucoside, Dicaprylyl Carbonate, Glycerin, Isocetyl Stearoyl Stearate, Isononyl Isononanoate, Methyl Dihydroabietate, Microcrystalline Cellulose, Polyester-8, Polyhydroxystearic Acid, Propanediol, Sclerocarya Birrea Seed Oil, Silica, Sodium Gluconate, Sodium Stearoyl Glutamate, Tocopherol, Water

OTHER SAFETY INFORMATION

- Protect the product in this container from excessive heat and direct sun
- Avoid spraying on facbrics - may cause discoloration

QUESTIONS

Contact Hi@oarsandalps.com